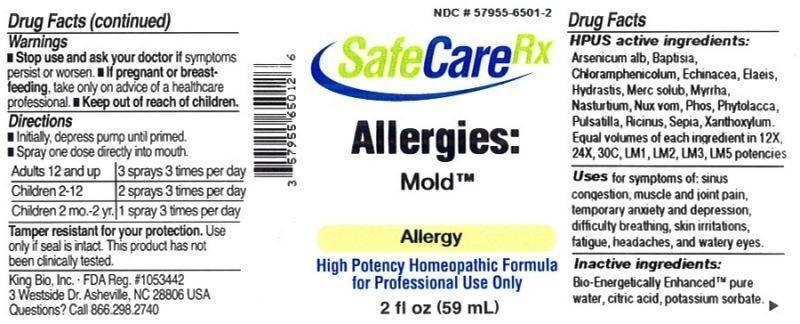 DRUG LABEL: Allergies Mold
NDC: 57955-6501 | Form: LIQUID
Manufacturer: King Bio Inc.
Category: homeopathic | Type: HUMAN OTC DRUG LABEL
Date: 20150812

ACTIVE INGREDIENTS: ARSENIC TRIOXIDE 12 [hp_X]/59 mL; BAPTISIA TINCTORIA ROOT 12 [hp_X]/59 mL; CHLORAMPHENICOL 12 [hp_X]/59 mL; ECHINACEA PURPUREA 12 [hp_X]/59 mL; ELAEIS GUINEENSIS FRUIT 12 [hp_X]/59 mL; GOLDENSEAL 12 [hp_X]/59 mL; MERCURIUS SOLUBILIS 12 [hp_X]/59 mL; MYRRH 12 [hp_X]/59 mL; NASTURTIUM OFFICINALE 12 [hp_X]/59 mL; STRYCHNOS NUX-VOMICA SEED 12 [hp_X]/59 mL; RICINUS COMMUNIS SEED 12 [hp_X]/59 mL; PHOSPHORUS 12 [hp_X]/59 mL; PHYTOLACCA AMERICANA ROOT 12 [hp_X]/59 mL; PULSATILLA VULGARIS 12 [hp_X]/59 mL; SEPIA OFFICINALIS JUICE 12 [hp_X]/59 mL; ZANTHOXYLUM AMERICANUM BARK 12 [hp_X]/59 mL
INACTIVE INGREDIENTS: WATER; POTASSIUM SORBATE; ANHYDROUS CITRIC ACID

Allergies: Mold

ACTIVE INGREDIENT

Drug Facts__________________________________________________________________________________________________________

HPUS active ingredients: Arsenicum album, Baptisia tinctoria, Chloramphenicolum, Echinacea purpurea, Elaeis guineensis, Hydrastis canadensis, Mercurius solubilis, Myrrha, Nasturtium aquaticum, Nux vomica,Phosphorus, Phytolacca decandra, Pulsatilla, Ricinus communis, Sepia, Xanthoxylum fraxineum. Equal volumes of each ingredient in 12X, 24X, 30C, LM1, LM2, LM3, LM5 potencies.

INDICATIONS AND USAGE

Uses for symptoms of: sinus congestion, muscle and joint pain, temporary anxiety and depression, difficulty breathing, skin irritations, fatigue, headaches, and watery eyes.

Inactive Ingredients:

Bio-Energetically Enhanced™ pure water, citric acid and potassium sorbate.

Warnings

- Stop use and ask your doctor if symptoms persist or worsen.
- If pregnant or breast-feeding, take only on advice of a healthcare professional.

- Keep out of reach of children.

Directions

- Initially, depress pump until primed.
- Spray one dose directly into mouth.
- Adults 12 and up: 3 sprays 3 times per day.
- Children 2-12: 2 sprays 3 times per day.
- Children 2 mo-2yr: 1 sprary 3 times per day.

OTHER SAFETY INFORMATION

Tamper resistant for your protection. Use only if seal is intact. This product has not been clinically tested.

PURPOSE

Uses for symptoms of:

- sinus congestion
- muscle and joint pain
- temporary anxiety and depression
- difficulty breathing
- skin irritations
- fatigue
- headaches
- watery eyes